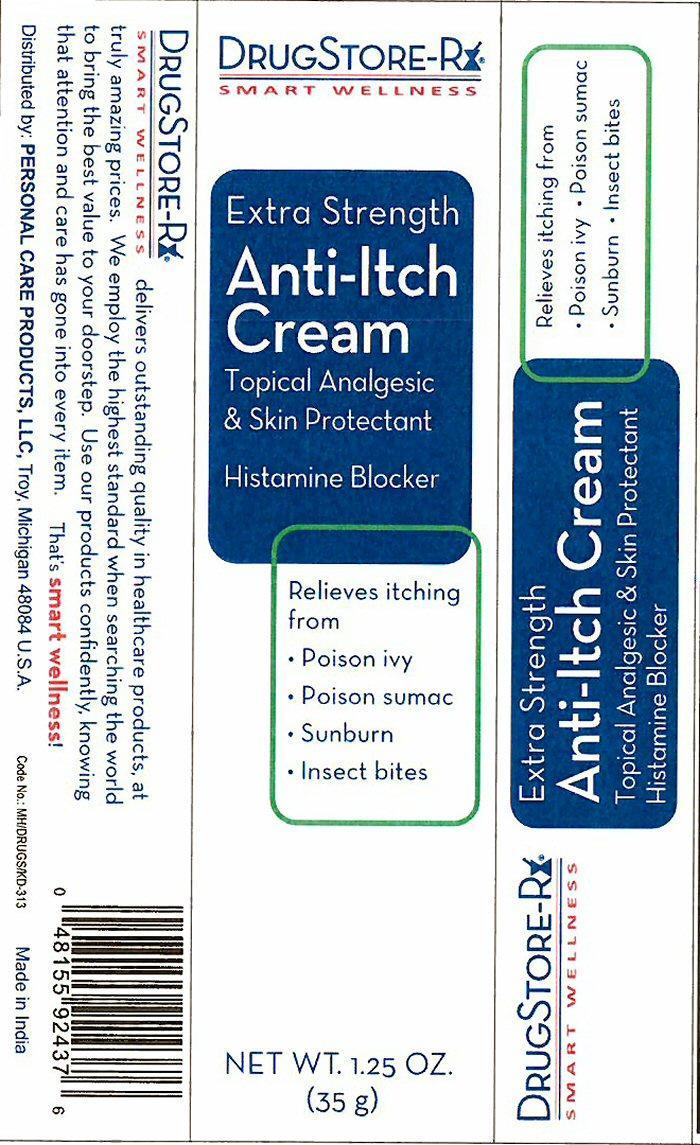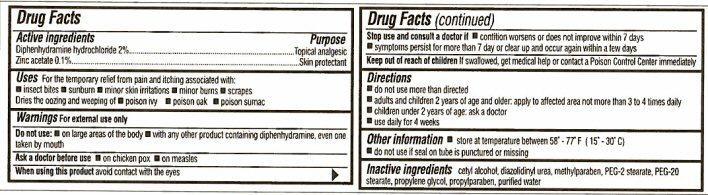 DRUG LABEL: Anti-Itch
NDC: 29500-2437 | Form: CREAM
Manufacturer: Personal Care Products, Inc.
Category: otc | Type: HUMAN OTC DRUG LABEL
Date: 20130711

ACTIVE INGREDIENTS: DIPHENHYDRAMINE HYDROCHLORIDE 700 mg/35 g; ZINC ACETATE 35 mg/35 g
INACTIVE INGREDIENTS: CETYL ALCOHOL; DIAZOLIDINYL UREA; METHYLPARABEN; PEG-2 STEARATE; PEG-20 STEARATE; PROPYLENE GLYCOL; PROPYLPARABEN ; WATER

Active ingredients

Drug Facts

Diphenhydramine hydrochloride 2%

Zinc acetate 0.1%

Purpose

Topical analgesic

Skin protectant

Keep out of reach of children. If swallowed, get medical help or contact a Poison Control Center immediately.

Uses

For the temporary relief from pain and itching associated with:

- insect bites
- sunburn
- minor skin irritations
- minor burns
- scrapes

Dries the oozing and weeping of

- poison ivy
- poison oak
- poison sumac

Warnings

For external use only
Do not use:

- on large areas of the body
- with any other product containing diphenhydramine, even one taken by mouth

Ask a doctor before use

- on chicken pox
- on measles

When using this product avoid contact with the eyes
Stop use and ask a doctor if

- condition worsens or does not improve within 7 days
- symptoms persist for more than 7 day or clear up and occur again within a few days

Directions

- do not use more than directed
- adults and children 2 years of age and older, apply to affected area not more than 3 to 4 times daily
- children under 2 years of age: ask a doctor
- use daily for 4 weeks

Other information

- store at temperature between 58° - 77° F (15° - 30° C)
- do not use if seal on tube is punctured or missing

Inactive ingredients

cetyl alcohol, diazolidinyl urea, methylparaben, PEG-2 stearate, PEG-20 stearate, propylene gylcol, propylparaben, purified water

Product Label

DRUGSTORE-Rx
SMART WELLNESS
Extra Strength
Anti-Itch Cream
Topical Analgesic and Skin Protectant
Histamine Blocker
Relieves itching from
* Poison ivy
* Poison sumac
* Sunburn
* Insect bites
NET WT. 1.25 OZ. (35 g)
DRUGSTORE-Rx
SMART WELLNESS delivers outstanding quality in healthcare products, at truly amazing prices. We employ the highest standard when searching the world to bring the best value to your doorstep. Use our products confidently, knowing that attention and care has gone into every item. That's smart wellness!
Distributed by: PERSONAL CARE PRODUCTS, LLC
Troy, Michigan 48084 U.S.A.
Code No. MH/DRUGS/KD-313 Made in India